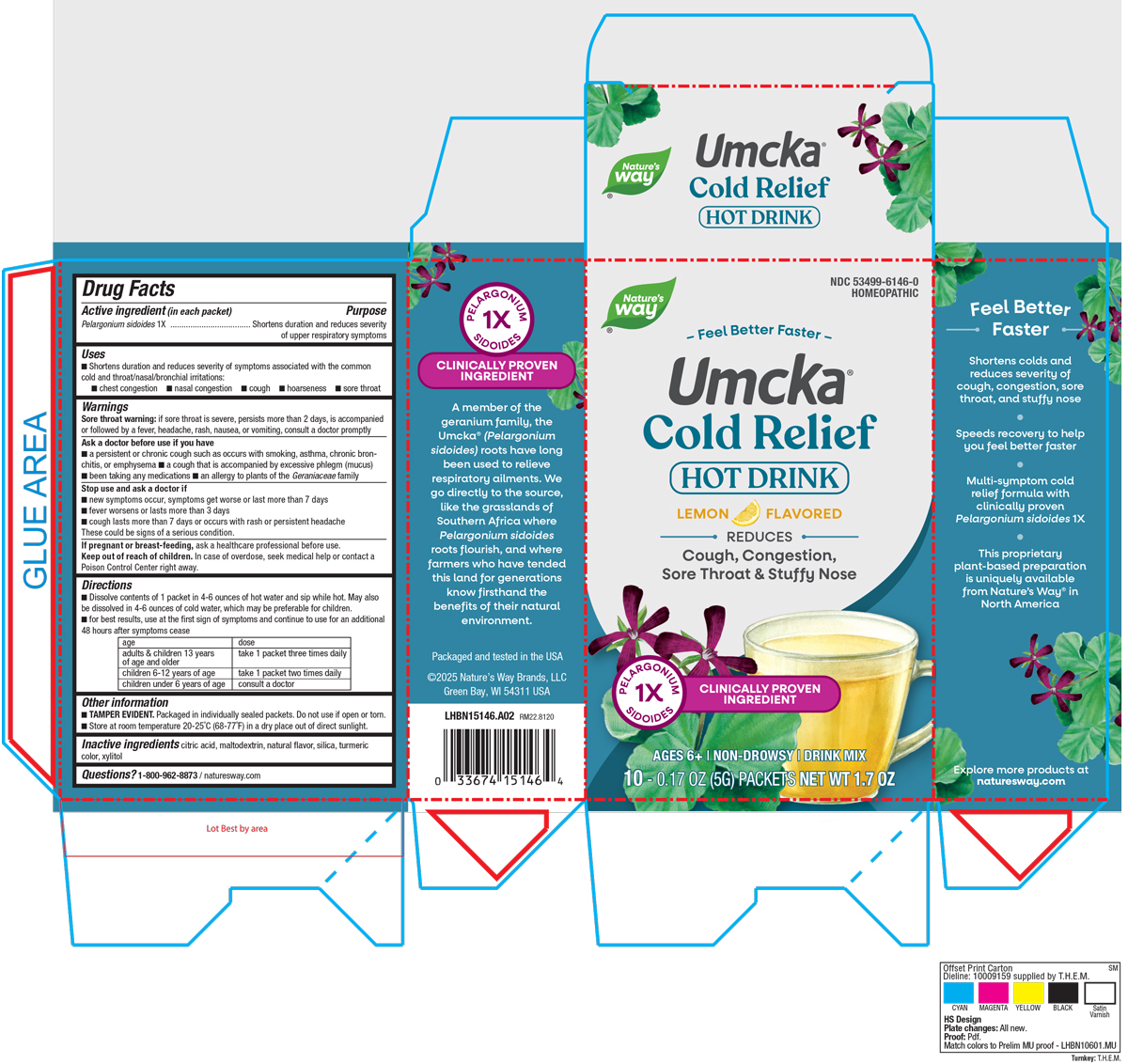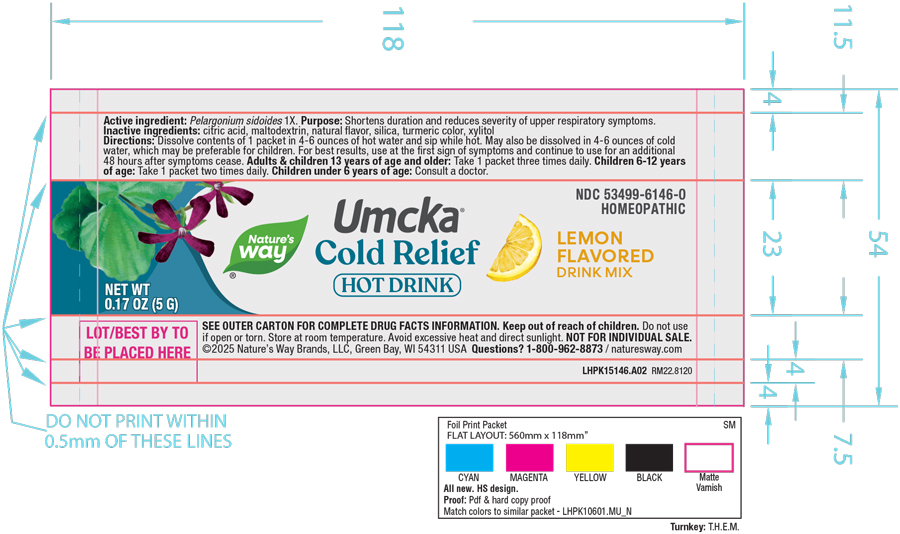 DRUG LABEL: Cold Relief Lemon
NDC: 53499-6146 | Form: POWDER
Manufacturer: Schwabe North America, Inc.
Category: homeopathic | Type: HUMAN OTC DRUG LABEL
Date: 20250731

ACTIVE INGREDIENTS: PELARGONIUM SIDOIDES ROOT 1 [hp_X]/5 g
INACTIVE INGREDIENTS: ANHYDROUS CITRIC ACID; MALTODEXTRIN; SILICON DIOXIDE; TURMERIC; XYLITOL

Cold Relief Lemon Hot Drink

Active Ingredient

Pelargonium sidoides 1X

Inactive Ingredients

Citric Acid

Maltodextrin

Natural Flavor

Silica

Turmeric Color

Xylitol

Dosage & Administration

Dissolve contents of 1 packet in 4-6 ounces of hot water and sip while hot.

May also be dissolved in 4-6 ounces of cold water, which may be preferable for children.
For best results, use at the first sign of symptoms and continue to use for an additional 48 hours after symptoms cease.
Adults and children 13 years of age and older: Take 1 packet three times daily.

Children 6-12 years of age: Take 1 packet two times daily.

Children under 6 years of age: Consult a doctor.

Indications & Usage

Shortens duration and reduces severity of symptoms associated with the common cold and throat/nasal/bronchial irritations: chest congestion, nasal congestion, cough, hoarseness, sore throat.

Purpose

Shortens duration and reduces severity of symptoms associated with the common cold and throat/nasal/bronchial irritations: chest congestion, nasal congestion, cough, hoarseness, sore throat.

Warnings

Sore throat warning: if sore throat is severe, persists more than 2 days, is accompanied or followed by a fever, headache, rash, nausea, or vomiting, consult a doctor promptly.

Ask Doctor

Ask a doctor before use if you have a persistent or chronic cough such as occurs with smoking, asthma, chronic bronchitis, or emphysema, a cough that is accompanied by excessive phlegm (mucus), been taking any medications, an allergy to plants of the Geraniaceae family.

Stop Use

Stop use and ask a doctor if new symptoms occur, symptoms get worse or last more than 7 days, fever worsens or lasts more than 3 days, cough lasts more than 7 days or occurs with rash or persistent headache.

These could be signs of a serious condition.

Pregnant or breast feeding

If pregnant or breast-feeding, ask a healthcare professional before use.

Keep out of reach of children

Overdose

In case of overdose, seek medical help or contact a Poison Control Center right away.